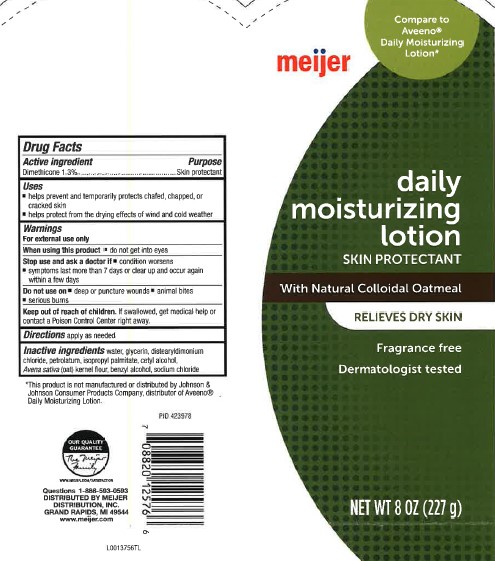 DRUG LABEL: Daily Moisturizing
NDC: 41250-619 | Form: LOTION
Manufacturer: Meijer, Inc.
Category: otc | Type: HUMAN OTC DRUG LABEL
Date: 20260219

ACTIVE INGREDIENTS: DIMETHICONE 13 mg/1 mL
INACTIVE INGREDIENTS: WATER; GLYCERIN; DISTEARYLDIMONIUM CHLORIDE; PETROLATUM; ISOPROPYL PALMITATE; CETYL ALCOHOL; OATMEAL; BENZYL ALCOHOL; SODIUM CHLORIDE

Meijer 619.003/619AC rev 2
Daily Moisturizing Lotion

Active ingredient

Dimethicone 1.3%

Purpose

Skin protectant

Uses

- helps prevent and temporarily protects chafed, chapped, or cracked skin.
- Helps protect from the drying effects of wind and cold weather

Warnings

For external use only

When using this product

- do not get into eyes

Stop use and ask a doctor if

- condition worsens
- symptoms last more than 7 days or clear up and occur again within a few days

Do not use on

- deep or punture wounds
- animal bites
- serious burns

Keep out or reach of children.

If swallowed, get medical help or contract a Poison Control Center right away.

Directions

apply as needed

Inactive ingredients

water, glycerin, distearyldimonium chloride, petrolatum, isopropyl palmitate, cetyl alcohol, Avena sativa (oat) kernel flour, benzyl alcohol, sodium chloride

Disclaimer

*This product is not manufactured or distributed by Johnson & Johnson Consumer Products Company, distributer of Aveeno® Daily Moisturizing Lotion.

Adverse reaction

OUR QUAILTY GUARANTEE

The Meijer Family

WWW.MEIJER.COM/SATISFACTION

Questions 1-888-593-0593

DISTRIBUTED BY MEIJER DISTRIBUTION, INC.

GRAND RAPIDS, MI 49544

www.meijer.com

principal display panel

meijer

Compare to Aveeno® Daily Moisturizing Lotion*

daily moisturizing lotion

SKIN PROTECTANT

With Natural Colloidal Oatmeal

RELIEVES DRY SKIN

Fragrance free

Dermatologist tested

NET WT 8 OZ (227 g)